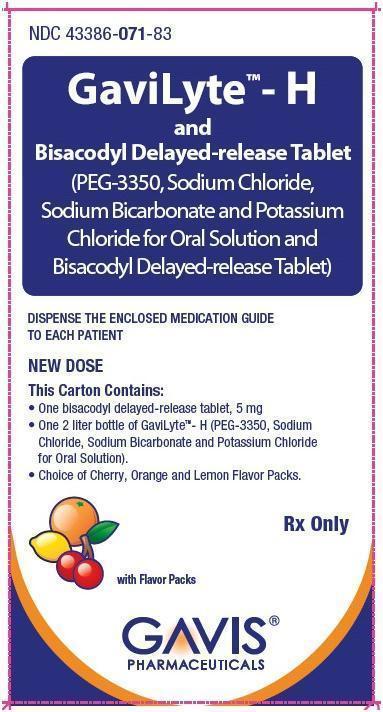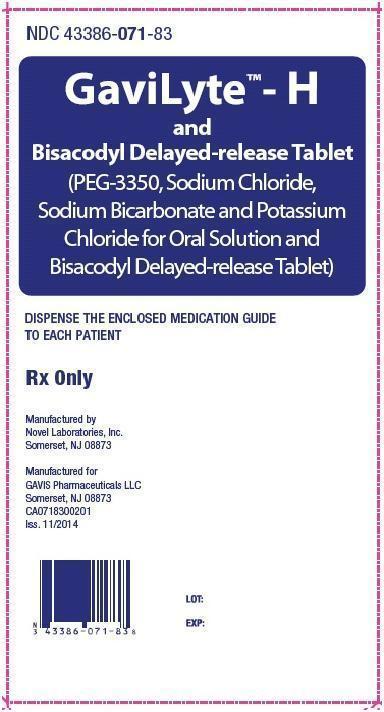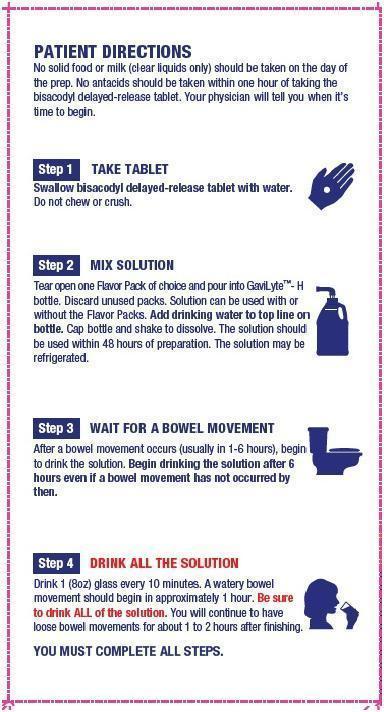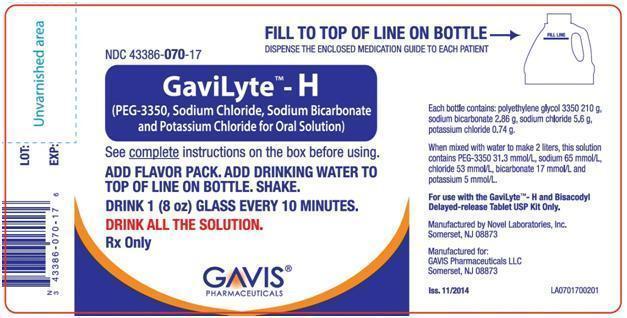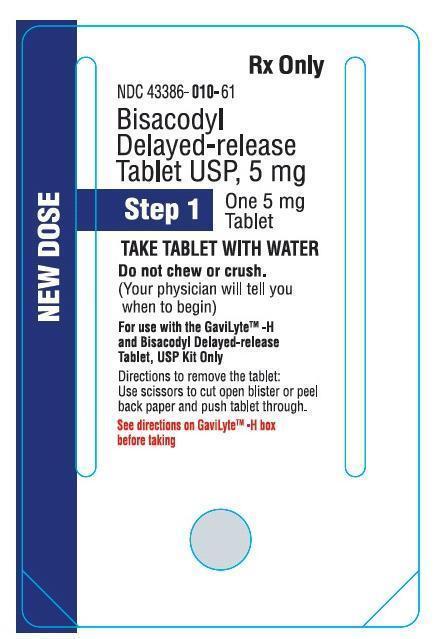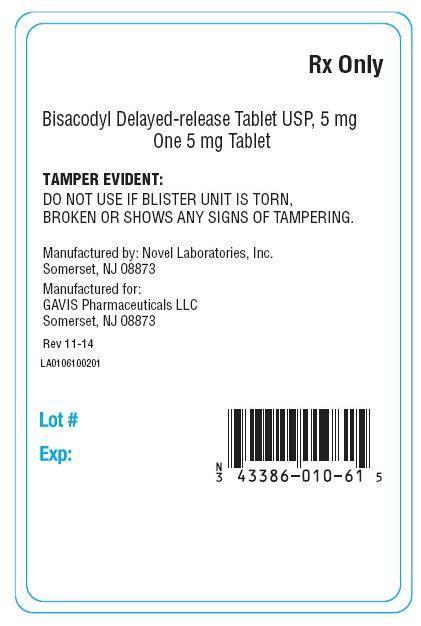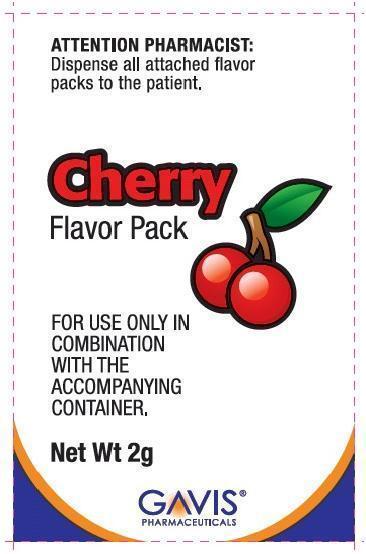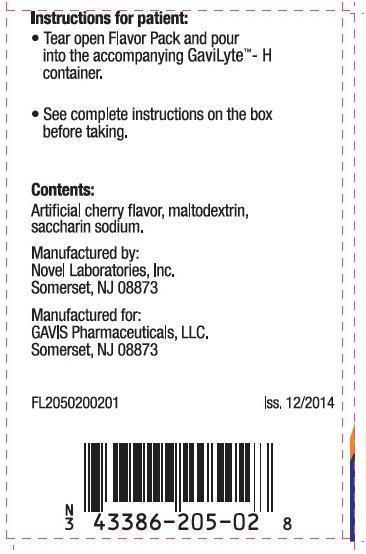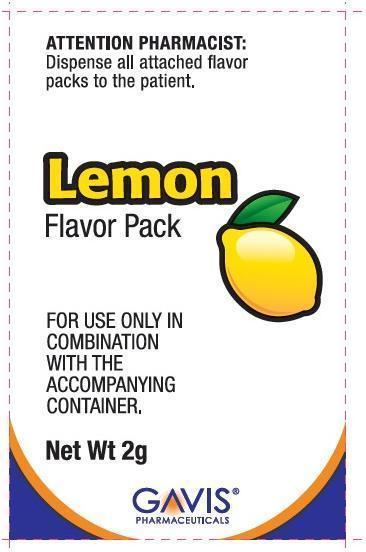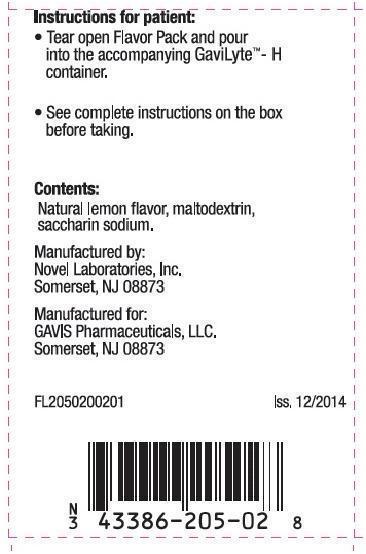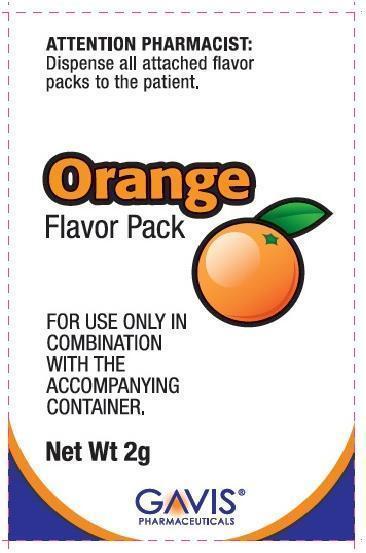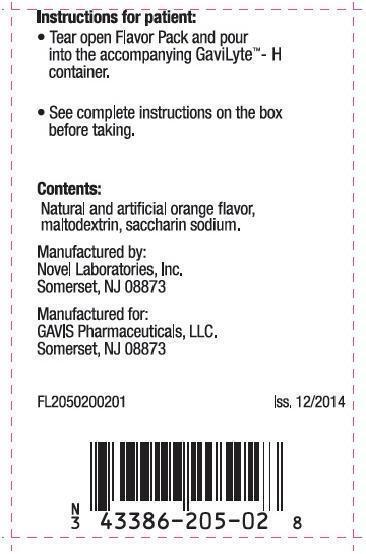 DRUG LABEL: GaviLyte-H and Bisacodyl
NDC: 43386-071 | Form: KIT | Route: ORAL
Manufacturer: Lupin Pharmaceuticals, Inc.
Category: prescription | Type: HUMAN PRESCRIPTION DRUG LABEL
Date: 20250128

ACTIVE INGREDIENTS: BISACODYL 5 mg/1 1; POLYETHYLENE GLYCOL 3350 210 g/2 L; SODIUM CHLORIDE 5.6 g/2 L; SODIUM BICARBONATE 2.86 g/2 L; POTASSIUM CHLORIDE 0.74 g/2 L
INACTIVE INGREDIENTS: ANHYDROUS LACTOSE; CELLULOSE, MICROCRYSTALLINE; CROSCARMELLOSE SODIUM; MAGNESIUM STEARATE; METHACRYLIC ACID; TALC; TITANIUM DIOXIDE; TRIETHYL CITRATE; D&C RED NO. 27; SILICON DIOXIDE; SODIUM BICARBONATE; SODIUM LAURYL SULFATE; FD&C BLUE NO. 2; FD&C YELLOW NO. 6; CHERRY; ORANGE; LEMON

HIGHLIGHTS OF PRESCRIBING INFORMATION

These highlights do not include all the information needed to use GaviLyte-H and Bisacodyl safely and effectively. See full prescribing information for GaviLyte-H and Bisacodyl.
GaviLyte-H and Bisacodyl (Polyethylene Glycol 3350, Sodium Chloride, Sodium Bicarbonate, Potassium Chloride and Bisacodyl Delayed release Tablet) KIT for ORAL use.
Initial U.S. Approval: 2004

1 INDICATIONS & USAGE

GaviLyte - H and bisacodyl delayed-release tablet, USP is a combination of PEG-3350, an osmotic laxative and bisacodyl, a stimulant laxative, indicated for cleansing of the colon as a preparation for colonoscopy in adults (1)

2 DOSAGE & ADMINISTRATION

See FULL PRESCRIBING INFORMATION for complete dosing and administration instructions (2)

- No solid food or milk (clear liquids only) should be consumed on the day of the preparation.
- Take one 5 mg bisacodyl tablet with water. Do NOT chew or crush.
- Dissolve the GaviLyte - H powder in 2 liters of water.
- Wait for a bowel movement (or maximum of 6 hours) then drink all the GaviLyte - H solution at a rate of 8 ounces every 10 minutes.
- Consume only clear liquids until the colonoscopy.

3 DOSAGE FORMS & STRENGTHS

- One 5 mg bisacodyl delayed-release tablet, USP (3)
- One 2 liter GaviLyte - H bottle with powder for reconstitution (3)

4 CONTRAINDICATIONS

- Gastrointestinal (GI) obstruction (4)
- Bowel perforation (4)
- Toxic colitis or toxic megacolon (4)
- Gastric retention (4)
- Ileus (4)

5 WARNINGS AND PRECAUTIONS

- Risk of fluid and electrolyte abnormalities, arrhythmias, seizures and renal impairment – assess concurrent medications and consider testing in some patients (5.1, 5.2, 5.3, 5.4)
- Patients with renal impairment – use caution, ensure adequate hydration and consider testing (5.3)
- Ischemic colitis has been reported (5.5)
- Suspected GI obstruction or perforation – rule out the diagnosis before administration (5.6)
- Patients at risk for aspiration – observe during administration (5.7)

6 ADVERSE REACTIONS

Most common adverse reactions (>3%) are overall discomfort, abdominal fullness, abdominal cramping, nausea, and vomiting, (6.1)

To report SUSPECTED ADVERSE REACTIONS, contact Novel Laboratories, Inc. at 908-603-6000 or FDA at 1-800-FDA-1088 or www.fda.gov/medwatch.

7 DRUG INTERACTIONS

- Some drugs (e.g., diuretics, angiotensin converting enzyme inhibitors, angiotensin receptor blockers, or non-steroidal anti-inflammatory drugs) increase risk due to fluid and electrolyte changes (7.1)
- Oral medication administered within one hour of the start of drinking GaviLyte - H might not be absorbed fully. (7.2)
- Do not take the bisacodyl tablet within one hour of taking antacid (7.3)

FULL PRESCRIBING INFORMATION

1 INDICATIONS & USAGE

GaviLyte - H and bisacodyl delayed-release tablet, USP is indicated for cleansing of the colon as a preparation for colonoscopy in adults.

2 DOSAGE & ADMINISTRATION

The recommended GaviLyte - H and bisacodyl delayed-release tablet, USP oral dosage regimen for adults on the day prior to colonoscopy is as follows:

- No solid food or milk (clear liquids only) should be consumed on the day of the preparation.
- Take one 5 mg bisacodyl delayed-release tablet, USP with water. Do NOT chew or crush the tablet.
- No antacids should be taken within one hour of taking the bisacodyl delayed-release tablet, USP.
- Prepare the GaviLyte - H solution according to the instructions on the kit.
- Add flavor pack of choice (if applicable) to the 2 liter container.
- No additional ingredients (other than flavor packs provided) should be added to the solution.
- Prepare the GaviLyte - H solution by filling the container to the 2 liter mark with water. Cap the container. Shake to dissolve the powder.
- Wait for a bowel movement (or maximum of 6 hours) then drink the 2 liter GaviLyte - H solution at a rate of 8 ounces every 10 minutes. Drink all of the solution.
- If you have abdominal distention or discomfort, stop drinking the GaviLyte - H solution temporarily or drink each portion at longer intervals until your symptoms improve.
- Consume only clear liquids after taking the GaviLyte - H solution until your colonoscopy.

3 DOSAGE FORMS & STRENGTHS

- One pink, round, enteric coated 5 mg bisacodyl delayed-release tablet, USP, de-bossed with “N1” on one side and plain on the other side.
- One 2 liter GaviLyte - H bottle with powder for reconstitution

4 CONTRAINDICATIONS

The GaviLyte - H and bisacodyl delayed-release tablet, USP is contraindicated in the following conditions:

- Gastrointestinal (GI) obstruction
- Bowel perforation
- Toxic colitis and toxic megacolon
- Gastric retention
- Ileus

5 WARNINGS AND PRECAUTIONS

5.1 Serious Fluid and Serum Chemistry Abnormalities

Advise all patients to hydrate adequately before, during, and after the use of GaviLyte - H and bisacodyl delayed-release tablet, USP. If a patient develops significant vomiting or signs of dehydration after taking GaviLyte - H and bisacodyl delayed-release tablet, USP, consider performing post-colonoscopy lab tests (electrolytes, creatinine, and BUN). Fluid and electrolyte disturbances can lead to serious adverse events including cardiac arrhythmias, seizures and renal impairment.

Patients with electrolyte abnormalities should have them corrected before treatment with GaviLyte - H and bisacodyl delayed-release tablet, USP. In addition, use caution when prescribing GaviLyte - H and bisacodyl delayed-release tablet, USP for patients with conditions, or who are using medications, that increase the risk for fluid and electrolyte disturbances or may increase the risk of adverse events of seizure, arrhythmias, and renal impairment.[See Drug Interactions (7.1)]

5.2 Seizures

There have been reports of generalized tonic-clonic seizures with the use of large volume (4 liter) PEG-based colon preparation products in patients with no prior history of seizures. The seizure cases were associated with electrolyte abnormalities (e.g., hyponatremia, hypokalemia, hypocalcemia, and hypomagnesemia) and low serum osmolality. The neurologic abnormalities resolved with correction of fluid and electrolyte abnormalities.

Use caution when prescribing the GaviLyte - H and bisacodyl delayed-release tablet, USP for patients with a history of seizures and in patients at risk of seizure, such as patients taking medications that lower the seizure threshold (e.g., tricyclic antidepressants), patients withdrawing from alcohol or benzodiazepines, patients with known or suspected hyponatremia, or patients using concomitant medications (such as diuretics) that increase the risk of electrolyte abnormalities. Monitor baseline and post-colonoscopy laboratory tests (sodium, potassium, calcium, creatinine, and BUN) in these patients.

5.3 Renal Impairment

Patients with impaired water handling who experience severe vomiting should be closely monitored including measurement of electrolytes (sodium, potassium, calcium, BUN and creatinine). Use caution when prescribing GaviLyte - H and bisacodyl delayed-release tablet, USP for patients with impaired renal function or patients taking concomitant medications that may affect renal function (such as diuretics, angiotensin converting enzyme inhibitors, angiotensin receptor blockers, or non-steroidal anti-inflammatory drugs). Advise these patients of the importance of adequate hydration and consider performing baseline and post-colonoscopy laboratory tests (electrolytes, creatinine, and BUN) in these patients.

5.4 Cardiac Arrhythmias

There have been rare reports of serious arrhythmias associated with the use of ionic osmotic laxative products for bowel preparation. Use caution when prescribing GaviLyte - H and bisacodyl delayed-release tablet, USP for patients at increased risk of arrhythmias (e.g. patients with a history of prolonged QT, uncontrolled arrhythmias, recent myocardial infarction, unstable angina, congestive heart failure, or cardiomyopathy). Pre-dose and post-colonoscopy ECGs should be considered in patients at increased risk of serious cardiac arrhythmias.

5.5 Ischemic Colitis

There have been reports of ischemic colitis in patients with use of GaviLyte - H and 20 mg bisacodyl delayed-release tablet, USP and GaviLyte - H and 10 mg bisacodyl delayed-release tablet, USP. If patients develop severe abdominal pain or rectal bleeding, patients should be evaluated as soon as possible.

5.6 Patients with Significant Gastrointestinal Disease

If gastrointestinal obstruction or perforation is suspected, perform appropriate diagnostic studies to rule out these conditions before administering GaviLyte - H and bisacodyl delayed-release tablet, USP

Use with caution in patients with severe active ulcerative colitis.

5.7 Aspiration

Use with caution in patients with impaired gag reflex and patients prone to regurgitation or aspiration. Such patients should be observed during administration of the GaviLyte - H and bisacodyl delayed-release tablet, USP solution.

6 ADVERSE REACTIONS

6.1 Clinical Studies Experience

Because clinical studies are conducted under widely varying conditions, adverse reaction rates observed in the clinical studies of a drug cannot be directly compared to rates in clinical studies of another drug and may not reflect the rates observed in practice.

In a clinical study of GaviLyte - H and (5 mg vs. 10 mg) bisacodyl delayed-release tablet, USP, overall discomfort, abdominal fullness, abdominal cramping, nausea, and vomiting, were the most common adverse reactions (>3%). The data in Table 1 reflects the 154 patients that received GaviLyte - H and 5 mg bisacodyl tablet vs. the 154 patients that received GaviLyte - H and 10 mg bisacodyl tablets. The GaviLyte - H and 5 mg bisacodyl delayed-release tablet, USP population was 29-87 years of age, 49% male, 51% female, 13% African American, 83% White, 5% Hispanic requiring a colonoscopy. The demographics of the comparator group were similar.

Table 1: Adverse Reactions Observed in at Least 3% of Randomized Patients
 | GaviLyte - H and 5 mg Bisacodyl Delayed-release Tablet, USP(N=154)] | GaviLyte - H and 10 mg Bisacodyl Delayed-release Tablet, USP(N=154)
Overall Discomfort | 57% | 66%
Abdominal fullness | 40% | 53%
Abdominal cramping | 38% | 46%
Nausea | 34% | 42%
Vomiting | 10% | 7%

6.2 Postmarketing Experience

The following adverse reactions have been identified during post approval use of GaviLyte - H and bisacodyl delayed-release tablet, USP. Because these reactions are reported voluntarily from a population of uncertain size, it is not always possible to reliably estimate their frequency or establish a causal relationship to drug exposure.

Allergic Reactions:
Cases of urticaria, rhinorrhea, dermatitis and anaphylactic reactions have been reported with PEG-based products.

Gastrointestinal:
There are isolated reports of serious post-marketing events following the administration of PEG-based products in patients over 60 years of age. These adverse reactions include upper GI bleeding from a Mallory-Weiss tear, esophageal perforation, asystole, and acute pulmonary edema after vomiting and aspirating the PEG-based solution. In addition, during administration of 4 liters of PEG-3350 colon cleansing preparation the following serious adverse reactions were seen: two deaths in end stage renal failure patients who developed diarrhea, vomiting and dysnatremia [see Warnings and Precautions (5.3) ].

Ischemic colitis has been reported with use of of GaviLyte - H and 20 mg and 10 mg bisacodyl delayed-release tablets, USP for colon preparation prior to colonoscopy. However, a causal relationship between these ischemic colitis cases and the use of GaviLyte - H and bisacodyl delayed-release tablets, USP has not been established.

Neurologic:
There have been reports of generalized tonic-clonic seizures associated with use of large volume (4 liter) PEG-based colon preparation products in patients with no prior history of seizures. Cases of dizziness and syncope have been reported [see Warnings and Precautions (5.1)] .

7 DRUG INTERACTIONS

7.1 Drugs That May Increase Risks of Fluid and Electrolyte Abnormalities

Use caution when prescribing GaviLyte - H and bisacodyl delayed-release tablet, USP for patients with conditions, or who are using medications, that increase the risk for fluid and electrolyte disturbances or may increase the risk of adverse events of seizure, arrhythmias, and prolonged QT in the setting of fluid and electrolyte abnormalities. Consider additional patient evaluations as appropriate [see Warnings and Precautions (5.1)] in patients taking these concomitant medications.

7.2 Potential for Altered Drug Absorption

Oral medication administered within one hour of the start of administration of GaviLyte - H solution may be flushed from the GI tract and the medication may not be absorbed completely.

7.3 Interaction with Antacids

Do not take the bisacodyl delayed-release tablet within one hour of taking an antacid.

8 USE IN SPECIFIC POPULATIONS

8.1 Pregnancy

Pregnancy Category C animal reproduction studies have not been conducted. It is not known whether GaviLyte - H and bisacodyl delayed-release tablet, USP can cause fetal harm when administered to a pregnant woman or can affect reproductive capacity. GaviLyte - H and bisacodyl delayed-release tablet, USP should be given to a pregnant or nursing woman only if clearly needed.

8.3 Nursing Mothers

It is not known whether this drug is excreted in human milk. Because many drugs are excreted in human milk, caution should be exercised when GaviLyte - H and bisacodyl delayed-release tablet, USP is administered to a nursing woman.

8.4 Pediatric Use

Safety and effectiveness in pediatric patients has not been established.

8.5 Geriatric Use

Of the 148 patients who took GaviLyte - H and 5 mg bisacodyl delayed-release tablet, USP in clinical trials, 42 (28%) were 65 years of age or older, while 10 (7%) were 75 years of age or older. The rates of success appear to be lower in patients 65 years and older [see Clinical Studies (14)] .

10 OVERDOSAGE

Using more than the recommended dosage of bisacodyl in conjunction with GaviLyte - H solution increases the frequency of common adverse events and may increase the risk of ischemic colitis [see Warnings and Precautions (5.5)] .

11 DESCRIPTION

GaviLyte - H and bisacodyl delayed-release tablet, USP consists of PEG-3350, an osmotic laxative and bisacodyl, a stimulant laxative. Each GaviLyte - H and 5 mg bisacodyl delayed-release tablet, USP (Polyethylene glycol (PEG) 3350, sodium chloride, sodium bicarbonate and potassium chloride for oral solution and bisacodyl delayed-release tablet) consists of one 2 liter bottle of GaviLyte – H (PEG-3350, sodium chloride, sodium bicarbonate and potassium chloride for oral solution) powder for reconstitution and one 5 mg bisacodyl, delayed-release tablet, USP.

- Bisacodyl delayed-release tablet, USP: Each pink, round, enteric coated bisacodyl delayed-release tablet, USP (debossed “N1”) contains 5 mg of bisacodyl, USP (C22H19NO4) with a molecular weight of 361.40. Inactive ingredients include lactose (anhydrous) NF, microcrystalline cellulose NF, croscarmellose sodium NF, magnesium stearate NF, methacrylic acid copolymer, talc, titanium dioxide, triethyl citrate, D&C red # 27/phloxine aluminum lake, colloidal anhydrous silica, sodium bicarbonate, sodium lauryl sulfate, FD&C blue # 2/indigo carmine aluminum lake and FD&C yellow # 6/sunset yellow FCF aluminum lake. The bisacodyl delayed-release tablet, USP is administered orally prior to drinking the GaviLyte - H [see Dosage and Administration (2)] .
- GaviLyte – H (PEG-3350, sodium chloride, sodium bicarbonate and potassium chloride for oral solution): A white powder for reconstitution containing 210 grams of PEG-3350, 2.86 grams of sodium bicarbonate, 5.6 grams of sodium chloride, 0.74 grams of potassium chloride and 2 grams of flavoring ingredients (if applicable). Flavor Packs are available in Cherry (containing artificial cherry flavor powder, maltodextrin and sodium saccharin), Lemon (containing natural lemon flavor powder, maltodextrin and sodium saccharin), and Orange (containing natural and artificial orange flavor powder, maltodextrin and sodium saccharin). This preparation can be used without the addition of a Flavor Pack. When dissolved in water to a volume of 2 liters, the GaviLyte - H solution is isosmotic, clear, and colorless. The GaviLyte - H solution is administered orally after taking the one bisacodyl delayed-release tablet, USP [see Dosage and Administration (2)] .

12 CLINICAL PHARMACOLOGY

12.1 Mechanism of Action

Polyethylene glycol (PEG), which is an osmotic agent, causes water to be retained within the gastrointestinal tract.

Bisacodyl is hydrolyzed by intestinal brush border enzymes and colonic bacteria to form an active metabolite [bis-(p-hydroxyphenyl) pyridyl-2 methane; (BHPM)] that acts directly on the colonic mucosa to produce colonic peristalsis.

12.2 Pharmacodynamics

The stimulant laxative effect of bisacodyl, together with the osmotic effect of the unabsorbed PEG when ingested with a large volume of water, produces watery diarrhea.

12.3 PharmacoKinetics

When taken orally, PEG 3350 is minimally absorbed.

Bisacodyl, which is a prodrug, is converted to its active metabolite BHPM by intestinal brush border enzymes and colonic bacteria. The pharmacokinetics of bisacodyl following oral administration of the bisacodyl tablet has not been adequately characterized.

13 NONCLINICAL TOXICOLOGY

13.1 Carcinogenesis, Mutagenesis, Impairment of Fertility

Long-term studies in animals have not been performed to evaluate the carcinogenic potential of GaviLyte - H and bisacodyl delayed-release tablet, USP. Studies to evaluate its potential for impairment of fertility or its mutagenic potential have not been performed.

14 CLINICAL STUDIES

The colon cleansing efficacy of GaviLyte - H and bisacodyl delayed-release tablet, USP (with 5 mg of bisacodyl) was evaluated in a randomized, single blind (endoscopist only), active-controlled, multicenter study. In this study, 293 adult patients were included in the efficacy analysis. Patients ranged in age from 19 to 87 years old (mean age 55 years old) with 55% female and 45% male patients. Race was distributed as follows: 83% White, 12% African American, 8% Hispanic or Latino, and 4% other.

Patients were randomized to one of the following two colon preparations: 1) GaviLyte - H and bisacodyl delayed-release tablet, USP [10 mg of bisacodyl tablets were given at noon on the day before colonoscopy followed by 2 liters of GaviLyte - H (after the first bowel movement or maximum of 6 hours)] at a rate of 8 ounces every 10 minutes and 2) a modified GaviLyte - H and bisacodyl delayed-release tablet, USP [containing a 5 mg bisacodyl tablet given at noon on the day before colonoscopy followed by 2 liters of GaviLyte - H (after the first bowel movement or maximum of 6 hours)] at a rate of 8 ounces every 10 minutes.

Patients were instructed to refrain from solid food and to have clear liquids on the day before colonoscopy. In addition, patients were instructed to consume nothing by mouth, except clear liquids, from the time the preparation was completed until after the colonoscopy was completed.

The primary efficacy endpoint was the proportion of patients with successful colon cleansing (assessed by the colonoscopists), see Table 2 below. Successful colon cleansing was defined as preparations that were graded excellent (no more than small bits of adherent feces/fluid) or good (small amounts of feces or fluid not interfering with the exam) by the colonoscopist.

Table 2: Proportion of Patients with Successful Colon Cleansing
 | GaviLyte - H and 5 mg Bisacodyl Delayed-release Tablet, USP (H5) |  | GaviLyte - H and 10 mg Bisacodyl Delayed-release Tablet, USP (H10) |  | Difference between treatment groups(H5 - H10)
 | % (n/N) | Two-sided 95% CI^1 | % (n/N) | Two-sided 95% CI^1 | Percent Difference % | Two-sided 95% CI for Percent Difference
All Patients | 78 (114/147) | (69.9, 84.0) | 80 (117/146) | (72.7, 86.3) | -2.0 | (-11.9, 6.8)
^1Confidence Interval (CI) for within treatment percent success is from an exact Chi Square test.

The proportion of patients with successful colon cleansing was similar between treatment groups. No differences in response rates by gender or race were noted in the GaviLyte - H and 5 mg bisacodyl group. In patients ≥ 65 years of age treated with the GaviLyte - H and 5 mg bisacodyl delayed-release tablet, USP the proportion with successful colon cleansing was 67% (n=28/42)[ 95% CI: (50.5, 80.4)].

16 HOW SUPPLIED/STORAGE AND HANDLING

Each GaviLyte - H and bisacodyl delayed-release tablet, USP contains:

One 5 mg bisacodyl delayed-release tablet, USP: pink, round, enteric coated, debossed “N1” on one side and plain on the other in a blister strip.

One 2 liter bottle of GaviLyte – H (PEG-3350, sodium chloride, sodium bicarbonate and potassium chloride for oral solution) powder for reconstitution containing 210 grams of polyethylene glycol (PEG) 3350, 2.86 grams of sodium bicarbonate, 5.6 grams of sodium chloride, 0.74 grams of potassium chloride, and 2 gram of flavoring ingredients (if applicable). After adding 2 liters of water, the reconstituted GaviLyte - H solution (clear and colorless) contains 31.3 mmol/L of PEG-3350, 65 mmol/L of sodium, 53 mmol/L of chloride, 17 mmol/L of bicarbonate and 5 mmol/L of potassium.

GaviLyte - H and bisacodyl delayed-release tablet, USP with Flavor Packs contain 3 packs (2 gram each Cherry, Lemon, and Orange flavors) NDC 43386-071-83.

Storage:
Store at 20-25°C (68-77°F). Excursions permitted between 15-30°C (59-86°F). The reconstituted GaviLyte – H solution, which may be refrigerated, should be used within 48 hours.

17 PATIENT COUNSELING INFORMATION

See Medication Guide

Information for Patients

- Ask patients to let you know if they have trouble swallowing or are prone to regurgitation or aspiration.
- Tell patients not to take other laxatives while they are taking GaviLyte - H and bisacodyl delayed-release tablet , USP
- Tell patients that if they experience severe bloating, distention or abdominal pain, the administration of the solution should be slowed or temporarily discontinued until the symptoms abate. Advise patients to report these events to their health care provider.
- Advise patients that if they have hives, rashes, or any allergic reaction, they should discontinue the medication and contact their health care provider. Medication should be discontinued until they speak to their physician.
- Instruct patients to contact their healthcare provider if they develop signs and symptoms of dehydration. [see Warnings and Precautions (5.1)].
- Inform patients that oral medication administered within one hour of the start of administration of GaviLyte - H may be flushed from the GI tract and the medication may not be absorbed completely.

Manufactured by:
Novel Laboratories, Inc.
Somerset, NJ 08873

Manufactured for:

GAVIS Pharmaceuticals, LLC

Somerset, NJ 08873

PI0701700201
Iss. 12/2014

Medication Guide

GaviLyte - H (GAV-ee-LITE-H) and Bisacodyl (BIS-a-CO-dil) Delayed-Release Tablet, USP.

(PEG-3350, sodium chloride, sodium bicarbonate and potassium chloride for oral solution and bisacodyl delayed-release tablet, USP)

Read this Medication Guide before you start taking GaviLyte - H and bisacodyl delayed-release tablet, USP. This information does not take the place of talking with your healthcare provider about your medical condition or your treatment.

What is the most important information I should know about GaviLyte - H and bisacodyldelayed-release tablet, USP?

GaviLyte - H and bisacodyl delayed-release tablet, USP and other osmotic bowel preparations can cause serious side effects, including: Serious loss of body fluid (dehydration) and changes in blood salts (electrolytes) in your blood. These changes can cause:

- seizures. This can happen even if you have never had a seizure.
- kidney problems
- abnormal heartbeats that can cause death

Your chance of having fluid loss and changes in body salts with GaviLyte - H and bisacodyl delayed-release tablet, USPis higher if you:

- have heart problems
- have kidney problems
- take water pills or non-steroidal anti-inflammatory drugs (NSAIDS)

Tell your healthcare provider right away if you have any of these symptoms of a loss of too much body fluid (dehydration) while taking GaviLyte - H and bisacodyldelayed-release tablet, USP:

- dizziness
- urinating less often than normal
- headache

See “What are the possible side effects of GaviLyte - H and bisacodyl delayed-release tablet, USP?” for more information about side effects.

What is GaviLyte - H and bisacodyl delayed-release tablet, USP?

GaviLyte - H and bisacodyl delayed-release tablet, USP is a prescription medicine used by adults to clean the colon before a colonoscopy. GaviLyte - H and bisacodyl delayed-release tablet, USP cleans your colon by causing you to have diarrhea. Cleaning your colon helps your healthcare provider see the inside of your colon more clearly during your colonoscopy. It is not known if GaviLyte - H and bisacodyl delayed-release tablet, USP is safe and effective in children.

Who should not take GaviLyte - H and bisacodyldelayed-release tablet, USP?

Do not take GaviLyte - H and bisacodyl delayed-release tablet, USP if your healthcare provider has told you that you have:

- a blockage in your bowel (obstruction)
- an opening in the wall of your stomach or intestine (bowel perforation)
- problems with food and fluid emptying from your stomach (gastric retention)
- a very dilated intestine (bowel)
- an allergy to any of the ingredients in GaviLyte - H and bisacodyl delayed-release tablet, USP. See the end of this leaflet for a complete list of ingredients in GaviLyte - H and bisacodyl delayed-release tablet, USP.

What should I tell my healthcare provider before taking GaviLyte - H and bisacodyldelayed-release tablet, USP?

Before you take GaviLyte - H and bisacodyldelayed-release tablet, USP tell your healthcare provider if you:

- have heart problems
- have stomach or bowel problems
- have ulcerative colitis
- have problems with swallowing or gastric reflux
- have a history of seizures
- are withdrawing from drinking alcohol
- have a low blood salt (sodium) level
- have kidney problems
- have any other medical conditions
- are pregnant. It is not known if GaviLyte - H and bisacodyl delayed-release tablet, USP will harm your unborn baby. Talk to your doctor if you are pregnant or plan to become pregnant.
- are breastfeeding or plan to breastfeed. It is not known if GaviLyte - H and bisacodyl delayed-release tablet, USP passes into your breast milk. You and your healthcare provider should decide if you will take GaviLyte - H and bisacodyl delayed-release tablet, USP while breastfeeding.

Tell your healthcare provider about all the medicines you take, including prescription and non-prescription medicines, vitamins, and herbal supplements.

GaviLyte - H and bisacodyl delayed-release tablet, USP may affect how other medicines work. Medicines taken by mouth may not be absorbed properly when taken within 1 hour before the start of GaviLyte - H and bisacodyl delayed-release tablet, USP.

Especially tell your healthcare provider if you take:

- medicines for blood pressure or heart problems
- medicines for kidney problems
- medicines for depression
- water pills (diuretics)
- non-steroidal anti-inflammatory medicines (NSAID) pain medicines
- laxatives
- antacids

Ask your healthcare provider or pharmacist for a list of these medicines if you are not sure if you are taking any of the medicines listed above. Know the medicines you take. Keep a list of them to show your healthcare provider and pharmacist when you get a new medicine.

How should I take GaviLyte - H and bisacodyldelayed-release tablet, USP?

See the Patient Directions on the outer product carton for dosing instructions. You must read, understand, and follow these instructions to take GaviLyte - H and bisacodyldelayed-release tablet, USPthe right way.

- Take GaviLyte - H and bisacodyl delayed-release tablet, USP exactly as your healthcare provider tells you to take it.
- Do not take other laxatives while taking GaviLyte - H and bisacodyl delayed-release tablet, USP.
- Do not take antacids within 1 hour of taking the bisacodyl tablet.
- Do not chew or crush the bisacodyl tablet. Take the tablet with water.
- Do not eat solid foods while taking GaviLyte - H and bisacodyl delayed-release tablet, USP. Only clear liquids are allowed while taking and after taking GaviLyte - H and bisacodyl delayed-release tablet, USP until your colonoscopy.
- Stop drinking GaviLyte - H temporarily or allow for longer time between each dose if you have stomach discomfort, pain or bloating until your symptoms improve.
- Stop taking GaviLyte - H and bisacodyl delayed-release tablet, USP and call your healthcare provider right away if you develop hives or a rash. These may be signs of an allergic reaction.

What are the possible side effects of GaviLyte - H and bisacodyldelayed-release tablet, USP?

GaviLyte - H and bisacodyl delayed-release tablet, USP can cause serious side effects, including:

- See “What is the most important information I should know about GaviLyte - H and bisacodyl delayed-release tablet, USP?”
- changes in certain blood tests. Your healthcare provider may do blood tests after you take GaviLyte - H and bisacodyl delayed-release tablet, USP to check your blood for changes. Tell your healthcare provider if you have any symptoms of too much fluid loss, including:
- vomiting
- nausea
- bloating
- dizziness
- stomach (abdominal) cramping
- headache
- urinate less than usual
- trouble drinking clear liquid
- heart problems. GaviLyte - H and bisacodyldelayed-release tablet, USP may cause irregular heartbeats.
- seizures
- decreased blood flow to the intestine (ischemic colitis). There have been reports of ischemic colitis in people who have taken GaviLyte - H and bisacodyl delayed-release tablet, USP at higher doses. Tell your healthcare provider right away if you have severe stomach (abdominal) pain or rectal bleeding. These may be symptoms of ischemic colitis.
  The most common side effects of GaviLyte - H and bisacodyl delayed-release tablet, USP include:
- discomfort
- bloating
- stomach (abdominal) cramping
- nausea
- vomiting

Tell your healthcare provider if you have any side effect that bothers you or that does not go away. These are not all the possible side effects of GaviLyte - H and bisacodyl delayed-release tablet, USP. For more information, ask your healthcare provider or pharmacist.

Call your doctor for medical advice about side effects. You may report side effects to FDA at 1-800-FDA-1088.

How should I store GaviLyte - H and bisacodyldelayed-release tablet, USP?

- Store GaviLyte - H and bisacodyl delayed-release tablet, USP at 20-25°C (68-77°F)., Excursions permitted between 15-30°C (59-86°F).
- GaviLyte - H solution that has been mixed with water may be refrigerated. Mixed solution should be taken within 48 hours.

Keep GaviLyte - H and bisacodyldelayed-release tablet, USP and all medicines out of the reach of children.

General information about the safe and effective use of GaviLyte - H and bisacodyldelayed-release tablet, USP.

Medicines are sometimes prescribed for purposes other than those listed in a Medication Guide. Do not use GaviLyte - H and bisacodyl delayed-release tablet, USP for a condition for which it was not prescribed. Do not give GaviLyte - H and bisacodyl delayed-release tablet, USP to other people, even if they are going to have the same procedure you are. It may harm them.

This Medication Guide summarizes the most important information about GaviLyte - H and bisacodyl delayed-release tablet, USP. If you would like more information, talk with your healthcare provider. You can ask your pharmacist or healthcare provider for information that is written for healthcare professionals.

What are the ingredients in GaviLyte - H and bisacodyldelayed-release tablet, USP?

Active ingredients bisacodyl tablet: bisacodyl.

Inactive ingredients bisacodyl tablet: lactose (anhydrous) NF, microcrystalline cellulose NF, croscarmellose sodium NF, magnesium stearate NF, methacrylic acid copolymer, talc, titanium dioxide, triethyl citrate, D&C red # 27/phloxine aluminum lake, colloidal anhydrous silica, sodium bicarbonate, sodium lauryl sulfate, FD&C blue # 2/indigo carmine aluminum lake and FD&C yellow # 6/sunset yellow FCF aluminum lake.

Active ingredients GaviLyte - H: polyethylene glycol 3350, sodium chloride, sodium bicarbonate, potassium chloride.

Inactive ingredients GaviLyte - H: cherry, lemon, and orange flavor packs.

Manufactured by:

Novel Laboratories, Inc.
Somerset, NJ 08873

Manufactured for:

GAVIS Pharmaceuticals LLC

Somerset, NJ 08873

This Medication Guide has been approved by the U.S. Food and Drug Administration.

PI0701700201
Iss. 12/2014

PACKAGE LABEL.PRINCIPAL DISPLAY PANEL

Carton

With Flavor Packs

Rx Only

New Dose

GaviLyte - H and bisacodyl delayed-release tablet, USP

Front Panel

Back Panel

Side Panel

2 Liter Bottle Label

GaviLyte - H and bisacodyl delayed-release tablet, USP

Blister

GaviLyte - H and bisacodyl delayed-release tablet, USP

Front

Back

Cherry - Flavor Pack

GaviLyte - H and bisacodyl delayed-release tablet, USP

Lemon - Flavor Pack

GaviLyte - H and bisacodyl delayed-release tablet, USP

Orange - Flavor Pack

GaviLyte - H and bisacodyl delayed-release tablet, USP